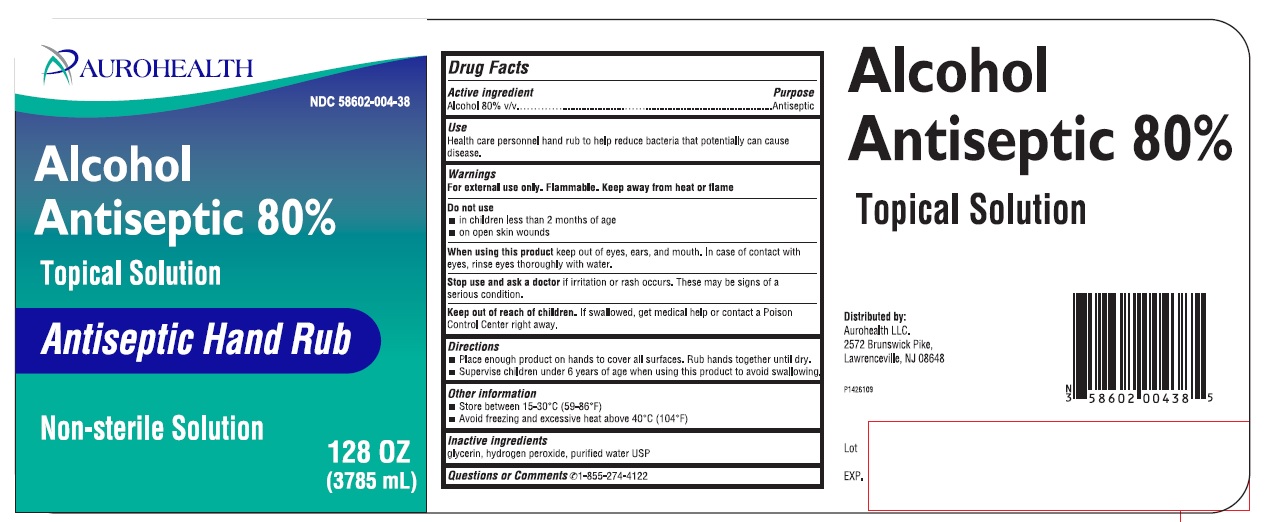 DRUG LABEL: Alcohol Antiseptic 80%
NDC: 58602-004 | Form: SOLUTION
Manufacturer: Aurohealth LLC
Category: otc | Type: Human OTC Drug Label
Date: 20200625

ACTIVE INGREDIENTS: ALCOHOL 80 mL/100 mL
INACTIVE INGREDIENTS: GLYCERIN; HYDROGEN PEROXIDE; WATER

Alcohol Antiseptic 80% Topical Solution
Antiseptic Hand Rub

ACTIVE INGREDIENT(S)

Alcohol 80% v/v

PURPOSE

Antiseptic

USE(S)

Health care personnel hand rub to help reduce bacteria that potentially causes disease.

WARNINGS

For external use only. Flammable. Keep away from heat or flame.

DO NOT USE

- in children less than 2 months of age
- on open skin wounds

When using this product keep out of eyes, ears, and mouth. In case of contact with eyes, rinse thoroughly with water.

STOP USE AND ASK DOCTOR IF

Stop using and ask doctor if irritation or rash occurs. These may be signs of a serious condition.

Keep out of reach of children. If swallowed, get medical help or contact a Poison Control Center right away.

DIRECTIONS

- Place enough product on hands to cover all surfaces. Rub hands together until dry.
- Supervise children under 6 years of age when using this product to avoid swallowing

OTHER INFORMATION

- Store between 15-30oC (59-86oF)
- Avoid freezing and excessive heat above 40oC (104oF)

INACTIVE INGREDIENT SECTION

glycerin, hydrogen peroxide, purified water USP

QUESTIONS OR COMMENTS

Call 1-855-274-4122

PRINCIPAL DISPLAY PANEL

AUROHEALTH
NDC 58602-004-38
Alcohol Aniseptic 80%
Topical Solution
Antiseptic Hand Rub
Non-sterile Solution
128 OZ (3785 mL)